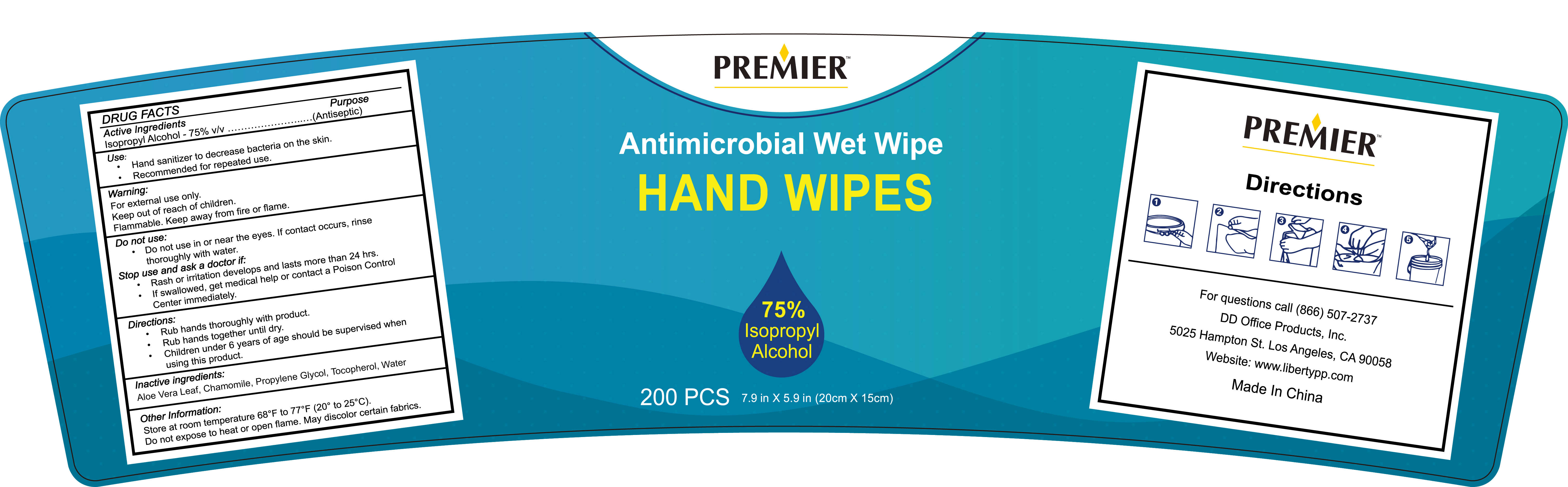 DRUG LABEL: 200 WET WIPES
NDC: 55415-009 | Form: CLOTH
Manufacturer: JIANGSU MEIFAN BIOTECHNOLOGY CO., LTD.
Category: otc | Type: HUMAN OTC DRUG LABEL
Date: 20201207

ACTIVE INGREDIENTS: ISOPROPYL ALCOHOL 0.594 kg/200 1
INACTIVE INGREDIENTS: PROPYLENE GLYCOL; WATER; CHAMOMILE; ALOE VERA LEAF; TOCOPHEROL

ACTIVE INGREDIENT

lsopropyl Alcohol - 75% v/v (Antimicrobial)

INACTIVE INGREDIENT

Aloe Vera Leaf, Chamomile,Propylene Glycol,Tocopherol, Water

Uses

Hand sanitizer to decrease bacteria on the skin.

Recommended for repeated use.

WARNINGS

For external use only.
Flammable. Keep away from fire or flame.

PURPOSE

Disinfection
Sterilization
No Rinseing

Do not use in or near the eyes. lf contact occurs, rinse thoroughly with water.

Stop use and ask a doctor if

Rash or irritation develops and lasts more than 24 hrs.

KEEP OUT OF REACH OF CHILDREN

lf swallowed, get medical help or contact a Poison Control Center immediately.

Directions

Rub hands thoroughly with product.

Rub hands together until dry.
Children under 6 years of age should be supervised when using this product.

Other Information

Store at room temperature 68°F to 77°F(20° to 25°C).

Do not expose to heat oropen flame. May discolor certain fabrics.